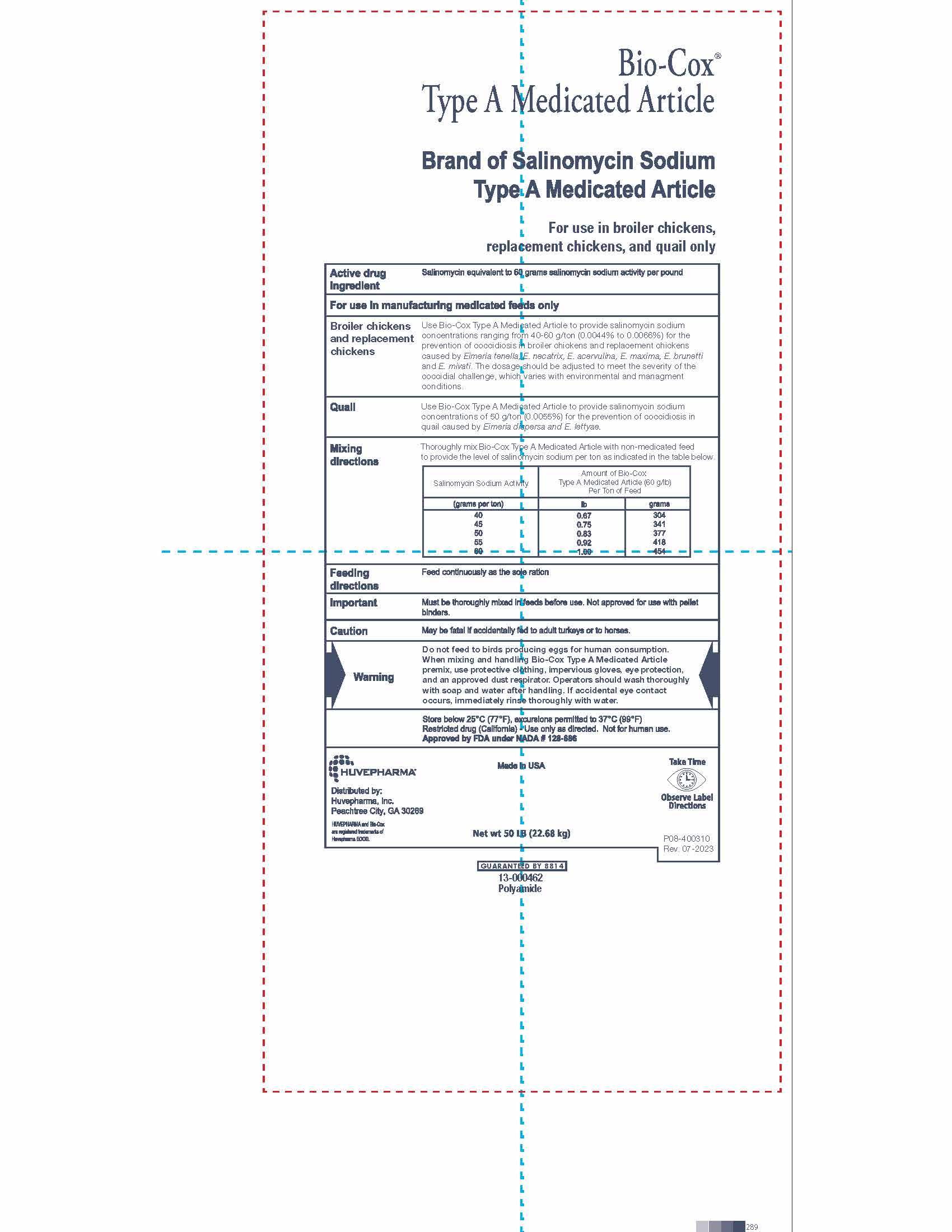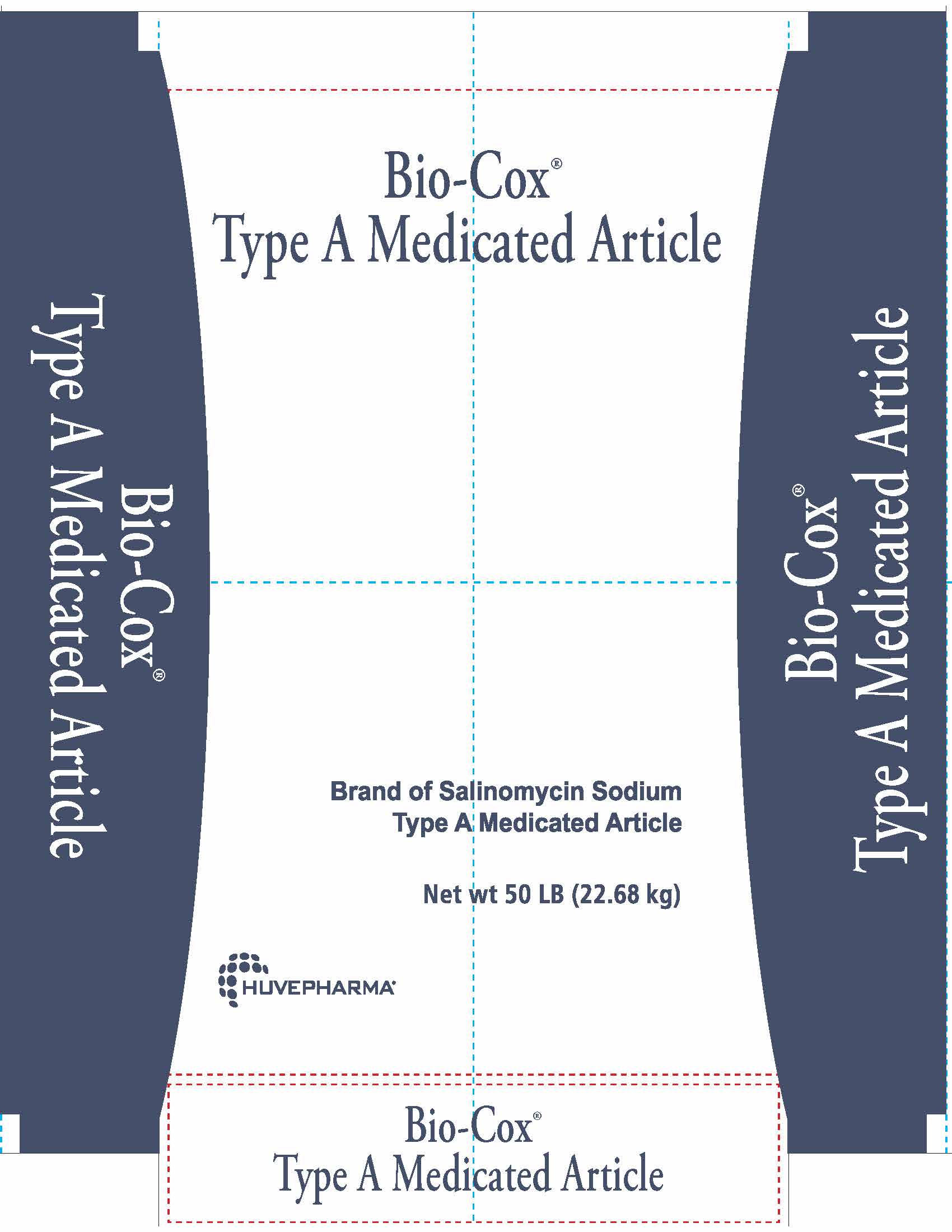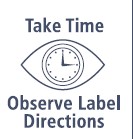 DRUG LABEL: Bio-Cox Type A Medicated Article
NDC: 23243-6807 | Form: POWDER
Manufacturer: Huvepharma, Inc.
Category: animal | Type: OTC TYPE A MEDICATED ARTICLE ANIMAL DRUG LABEL
Date: 20230913

ACTIVE INGREDIENTS: SALINOMYCIN SODIUM 60 g/0.45 kg

Bio-Cox®

Type A Medicated Article

Brand of Salinomycin Sodium
Type A Medicated Article

Net wt 50 LB (22.68 kg)

HUVEPHARMA®

DOSAGE AND ADMINISTRATION

Bio-Cox®
Type A Medicated Article

Brand of Salinomycin Sodium
Type A Medicated Article

For use in broiler chickens, replacement chickens, and quail only

Active drug ingredient

Salinomycin equivalent to 60 grams salinomycin sodium activity per pound

For use in manufacturing medicated feeds only

VETERINARY INDICATIONS

Broiler chickens and replacement chickens

Use Bio-Cox Type A Medicated Article to provide salinomycin sodium
concentrations ranging from 40-60 g/ton (0.0044% to 0.0066%) for the
prevention of coccidiosis in broiler chickens and replacement chickens
caused by Eimeria tenella, E. necatrix, E. acervulina, E. maxima, E. brunetti
and E. mivati. The dosage should be adjusted to meet the severity of the
coccidial challenge, which varies with environmental and managment
conditions.

Quail

Use Bio-Cox Type A Medicated Article to provide salinomycin sodium
concentrations of 50 g/ton (0.0055%) for the prevention of coccidiosis in
quail caused by Eimeria dispersa and E. lettyae.

INDICATIONS AND USAGE

Mixing directions

Thoroughly mix Bio-Cox Type A Medicated Article with non-medicated feed
to provide the level of salinomycin sodium per ton as indicated in the table below.

Salinomycin Sodium Activity | Amount of Bio-Cox Type A Medicated Article (60 g/lb) Per Ton of Feed
(grams per ton) | lb | grams
40; 45; 50; 55; 60 | 0.67; 0.75; 0.83; 0.92; 1.00 | 304; 341; 377; 418; 454

Feeding directions

Feed continuously as the sole ration

Important

Must be thoroughly mixed in feeds before use. Not approved for use with
pellet binders.

PRECAUTIONS

Caution

May be fatal if accidentally fed to adult turkeys or to horses.

Warning

Do not feed to birds producing eggs for human consumption.
When mixing and handling Bio-Cox Type A Medicated Article
premix, use protective clothing, impervious gloves, eye protection,
and an approved dust respirator. Operators should wash thoroughly
with soap and water after handling. If accidental eye contact
occurs, immediately rinse thoroughly with water.

STORAGE AND HANDLING

Store below 25°C (77°F), excursions permitted to 37°C (99°F)
Restricted drug (California) - Use only as directed. Not for human use.
Approved by FDA under NADA # 128-686

HUVEPHARMA®

Distributed by:
Huvepharma, Inc.
Peachtree City, GA 30269

HUVEPHARMA and Bio-Cox are registered trademarks of Huvepharma EOOD.

Made in USA

Net wt 50 LB (22.68 kg)